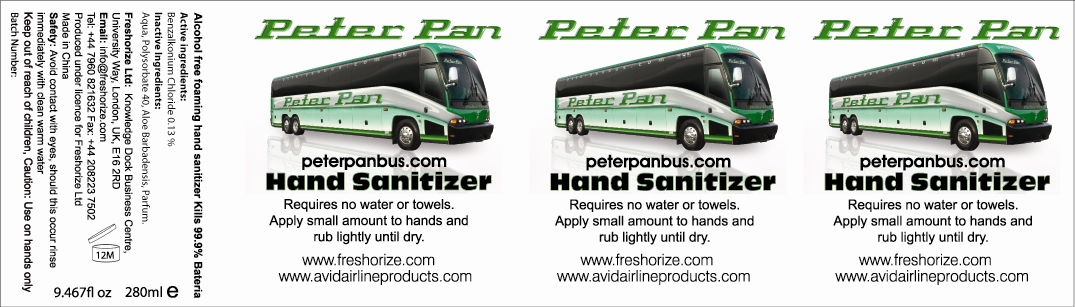 DRUG LABEL: Peter Pan
NDC: 52305-400 | Form: LOTION
Manufacturer: Freshorize, Ltd.
Category: otc | Type: HUMAN OTC DRUG LABEL
Date: 20110120

ACTIVE INGREDIENTS: Benzalkonium Chloride .364 g/280 mL
INACTIVE INGREDIENTS: Water; POLYSORBATE 40; ALOE VERA FLOWER

Drug Facts

Active Ingredients

E0.13% Benzylkonium Chloride

INDICATIONS AND USAGE

Requires no water or towels. Apply small amount to hands and rub lightly until dry.

WARNINGS

Safety: Avoid contact with Eyes, should this occur rinse immediately with clean warm water.
Caution: Use on hands only.

Keep out of reach of children.

PURPOSE

Kills 99.9% Bacteria

DOSAGE AND ADMINISTRATION

Requires no water or towels.
Apply small amount to hands and rub lightly until dry.

INACTIVE INGREDIENT

Aqua, Polysorbate 40, Aloe Barbadensis, Parfum